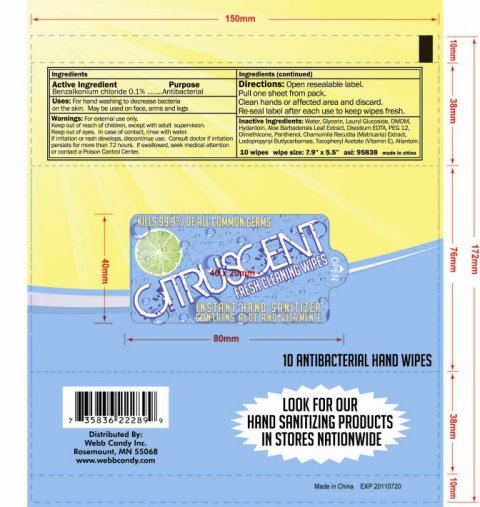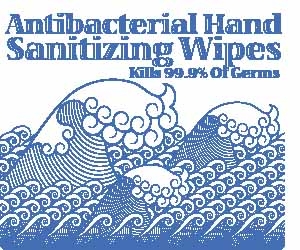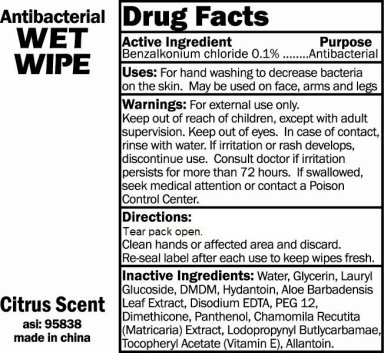 DRUG LABEL: Citrus Scent Antibacterial Hand Wipe
NDC: 49701-4000 | Form: SWAB
Manufacturer: The Webb Company 
Category: otc | Type: HUMAN OTC DRUG LABEL
Date: 20091124

ACTIVE INGREDIENTS: BENZALKONIUM CHLORIDE 0.1 1/1 1
INACTIVE INGREDIENTS: WATER; GLYCERIN; ALOE VERA LEAF; EDETATE DISODIUM; DIMETHICONE; PANTHENOL; CHAMOMILLA FLOWER; IODOPROPYNYL BUTYLCARBAMATE; ALPHA-TOCOPHEROL; ALLANTOIN

Citrus Scent Antibacterial Hand Wipe

Active Ingredient Purpose

Benzalkonium chloride 0.1 percent Antibacterial

PURPOSE

Uses: For hand washing to decrease bacteria on the skin.

May be used on face, arms and legs

Warnings: For external use only.

Keep out of reach of children, except with adult supervision. Keep out of eyes. In case of contact, rinse with water.

If irritation or rash develops, discontinue use. Consult doctor if irritation persists for more than 72 hours.

If swallowed, seek medical attention or contact a Poison Control Center.

Directions:

Tear pack open.

Clean hands or affected area and discard.

Re-seal label after each use to keep wipes fresh.

Directions:

Open resealable label.

Pull one sheet from pack.

Clean hands or affected area and discard.

Re-seal label after each use to keep wipes fresh.

INACTIVE INGREDIENT

Inactive Ingredients: Water, Glycerin, Lauryl Glucoside, DMDM, Hydantoin, Aloe Barbadensis Leaf Extract, Disodium EDTA, PEG 12,

Dimethicone, Panthenol, Chamomila Recutita (Matricaria) Extract, Lodopropynyl Butlycarbamae, Tocopheryl Acetate (Vitamin E), Allantoin

DESCRIPTION

10 wipes wipe size: 7.9 inches x 5.5 inches asi 95838 Made in China

PACKAGE LABEL

CITRUSCENT

FRESH CLEANING WIPES

INSTANT HAND SANITIZER

CONTAINS ALOE AND VITAMIN E

KILLS 99.9 PERCENT OF ALL COMMON GERMS

LOOK FOR OUR HAND SANITIZING PRODUCTS IN STORES NATIONWIDE

DISTRIBUTED BY

Webb Candy Inc.

Rosemount, MN 55068

www.webbcandy.com

Made In China

10 ANTIBACTERIAL HAND WIPES

PACKAGE LABEL

Antibacterial Hand Sanitizing Wipes

Kills 99.9 percent of germs

Antibacterial Wet Wipe

Citrus Scent

asi: 95838

Made in China